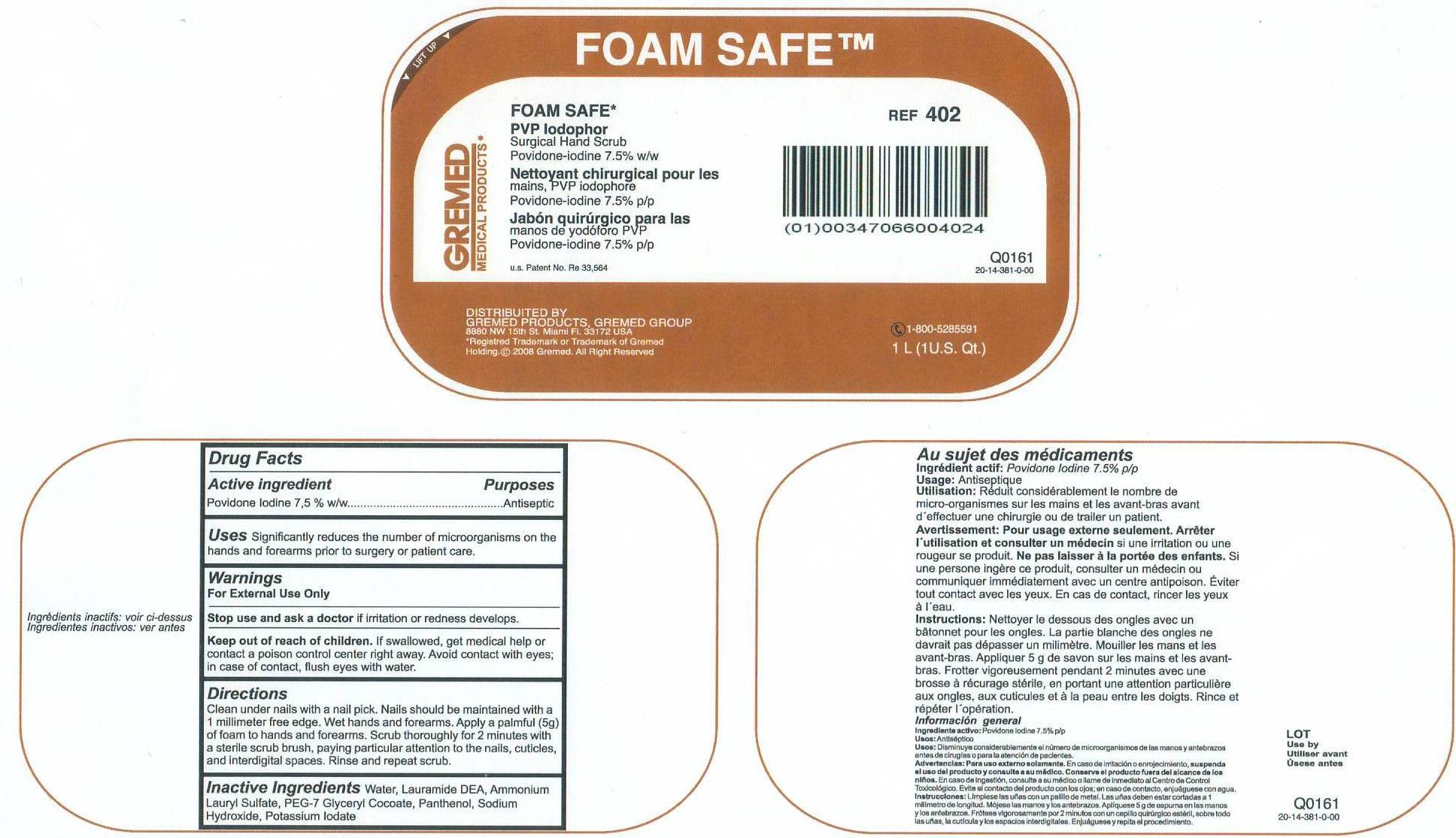 DRUG LABEL: Foam Safe
NDC: 47066-402 | Form: LIQUID
Manufacturer: Gremed Manufacturing LLC
Category: otc | Type: HUMAN OTC DRUG LABEL
Date: 20120417

ACTIVE INGREDIENTS: POVIDONE-IODINE 7.5 mg/100 mL
INACTIVE INGREDIENTS: WATER; LAURIC DIETHANOLAMIDE; AMMONIUM LAURYL SULFATE; POLYETHYLENE GLYCOL 350; GLYCERYL COCOATE; PANTHENOL; SODIUM HYDROXIDE; POTASSIUM IODATE

DRUG FACTS

Active Ingredient Purposes

Povidone Iodine 7.5% w/w .............. Antiseptic

Uses

Significantly reduces the number of microorganisms on the hands and forearms prior to surgery or patient care.

Warnings

For External Use Only

Stope use and ask doctor if irritation or redness develops.

Keep out of reach of children.

Directions

Clean under nails with a nail pick. Nails should be maintained with a 1 millimeter free edge. Wet hands and forearms. Apply a palmful (5g) of foam to hands and forearms. Scrub thoroughly for 2 minutes with a sterile scrub brush, paying particular attention to the nails, cuticles and interdigital spaces. Rinse and repeat scrub.

Inactive Ingredients

Water, Lauramide DEA, Ammonium Lauryl Sulfate, PEG-7, Glyceryl Cocoate, Panthenol, Sodium Hydroxide, Potassium Iodate

INDICATIONS AND USAGE

If swallowed, get medical help or contact a poison control center right away. Avoid contact with eyes; in case of contact, flush eyes with water.